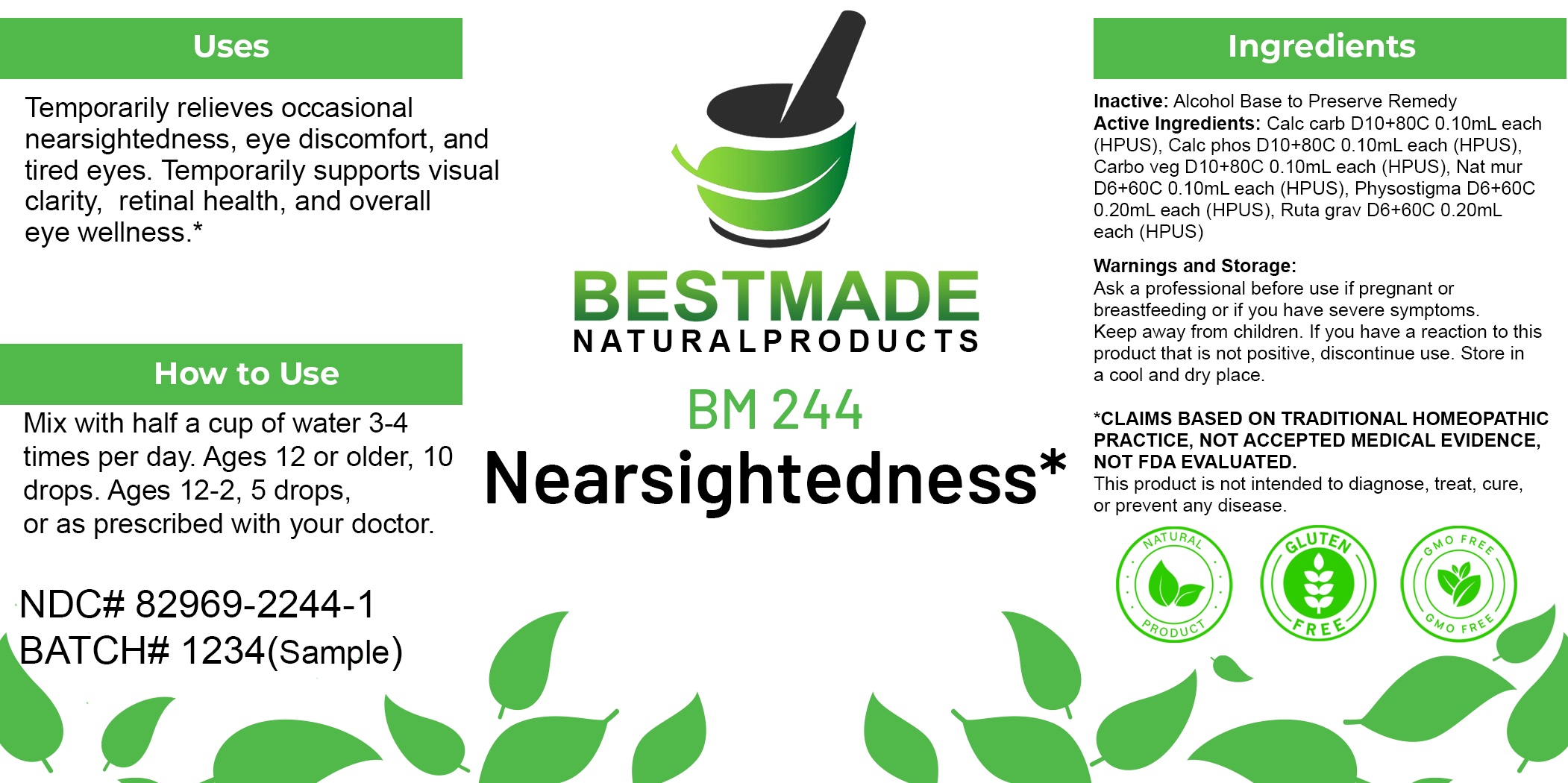 DRUG LABEL: Bestmade Natural Products BM244
NDC: 82969-2244 | Form: LIQUID
Manufacturer: Bestmade Natural Products
Category: homeopathic | Type: HUMAN OTC DRUG LABEL
Date: 20250304

ACTIVE INGREDIENTS: SODIUM CHLORIDE 30 [hp_C]/30 [hp_C]; OYSTER SHELL CALCIUM CARBONATE, CRUDE 30 [hp_C]/30 [hp_C]; TRIBASIC CALCIUM PHOSPHATE 30 [hp_C]/30 [hp_C]; PHYSOSTIGMA VENENOSUM SEED 30 [hp_C]/30 [hp_C]; ACTIVATED CHARCOAL 30 [hp_C]/30 [hp_C]; RUTA GRAVEOLENS FLOWERING TOP 30 [hp_C]/30 [hp_C]
INACTIVE INGREDIENTS: ALCOHOL 30 [hp_C]/30 [hp_C]

BM244

DOSAGE AND ADMINISTRATION

How to Use

Mix with half a cup of water 3-4 times per day. Ages 12 or older, 10 drops. Ages 12-2, 5 drops. Ages 2 and under, consult your Doctor.

Inactive:

Alcohol Base to Preserve Product

KEEP OUT OF REACH OF CHILDREN

Warnings and Storage:

Ask a professional before use if pregnant or breastfeeding or if you have severe symptoms.

Keep away from children. If you have a reaction to this product that is not positive, discontinue use. Store in a cool and dry place

*CLAIMS BASED ON TRADITIONAL HOMEOPATHIC PRACTICE, NOT ACCEPTED MEDICAL EVIDENCE NOT FDA EVALUATED.
This product is not intended to diagnose, treat, cure, or prevent any disease.

Warnings and Storage:

Ask a professional before use if pregnant or breastfeeding or if you have severe symptoms.

Keep away from children. If you have a reaction to this product that is not positive, discontinue use. Store in a cool and dry place

*CLAIMS BASED ON TRADITIONAL HOMEOPATHIC PRACTICE, NOT ACCEPTED MEDICAL EVIDENCE NOT FDA EVALUATED.
This product is not intended to diagnose, treat, cure, or prevent any disease.

Uses
Temporarily relieves occasional nearsightedness, eye discomfort, and tired eyes. Temporarily supports visual clarity, retinal health, and overall eye wellness.*

ACTIVE INGREDIENTS:

Calc carb D10+80C 0.10mL each (HPUS), Calc phos D10+80C 0.10mL each (HPUS), Carbo veg D10+80C 0.10mL each (HPUS), Nat mur D6+60C 0.10mL each (HPUS), Physostigma D6+60C 0.20mL each (HPUS), Ruta grav D6+60C 0.20mL each (HPUS)

Uses
Temporarily relieves occasional nearsightedness, eye discomfort, and tired eyes. Temporarily supports visual clarity, retinal health, and overall eye wellness.*

Entire package label